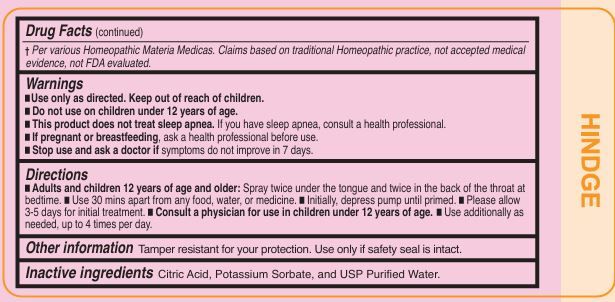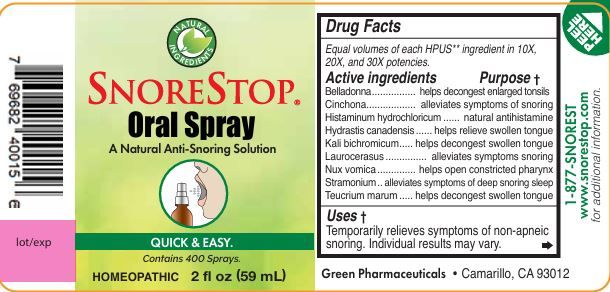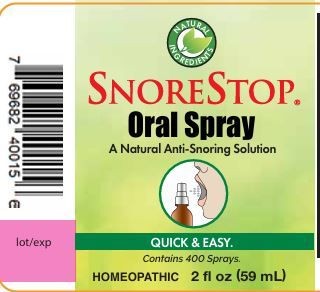 DRUG LABEL: Snorestop
NDC: 61152-600 | Form: SPRAY
Manufacturer: Green Pharmaceuticals Inc
Category: homeopathic | Type: HUMAN OTC DRUG LABEL
Date: 20250819

ACTIVE INGREDIENTS: PRUNUS LAUROCERASUS LEAF 10 [hp_X]/59 mL; CINCHONA BARK 10 [hp_X]/59 mL; STRYCHNOS NUX-VOMICA SEED 10 [hp_X]/59 mL; HYDRASTIS CANADENSIS WHOLE 10 [hp_X]/59 mL; ATROPA BELLADONNA 10 [hp_X]/59 mL; HISTAMINE DIHYDROCHLORIDE 10 [hp_X]/59 mL; TEUCRIUM MARUM 10 [hp_X]/59 mL; DATURA STRAMONIUM 10 [hp_X]/59 mL; POTASSIUM DICHROMATE 10 [hp_X]/59 mL
INACTIVE INGREDIENTS: POTASSIUM SORBATE; WATER; ANHYDROUS CITRIC ACID

Snorestop Oral Spray 59ml

Ingredients (HPUS):

Equal volumes of each HPUS ingredient in 10X, 30X.

Nux vomica 10X, 20X, & 30X, Belladonna 10X, 20X, & 30X, Hydrastis canadensis 10X, 20X, & 30X, Kali bichromicum 10X, 20X, & 30X, Teucrium marum 10X, 20X, & 30X, Histaminum hydrochloricum 10X, 20X, & 30X, Laurocerasus 10X, 20X, & 30X, Cinchona10X, 20X, & 30X, Stramonium 10X, 20X, & 30X.

Inactive Ingredients:

Citric Acid
Potassium Sorbate
USP Purified Water

Uses:

Temporarily relieves symptoms of non-apneic snoring. Individual results may vary.

Warnings:

Use only as directed. Keep out of reach of children.
Do not use on children under 12 years of age.
This product does not treat sleep apnea. If you have sleep apnea,consult a health professional.
If pregnant or breastfeeding, ask a health professional before use.
Stop use and ask a doctor if symptoms do not improve in 7 days.

Keep out of reach of children.

Directions:

Adults and children 12 years of age and older: Spray twice under the tongue and twice in the back of the throat at bedtime.

Use 30 mins apart from any food, water, or medicine.

Initially, depress pump until primed.

Please allow 3-5 days for initial treatment.

Consult a physician for use in children under 12 years of age.

Use additionally as needed, up to 4 times per day.

Purpose:

Temporarily helps stop or reduce symptoms of non-apneic snoring. Individual results may vary.

Other information

Tamper resistant for your protection. Use only if safety seal is intact.

Questions?

1-877-SNORESTOP

www.snorestop.com

RECENT MAJOR CHANGES

Indications and Usage

Warnings and Precautions

Dosage and Administration

PACKAGE LABEL

Snorestop Oral Spray

A Natural Anti-Snoring solution

Quick & Easy

Contains 400 Sprays

Homeopathic 2fl oz (59ml)

UPC 7 69682 40015 6